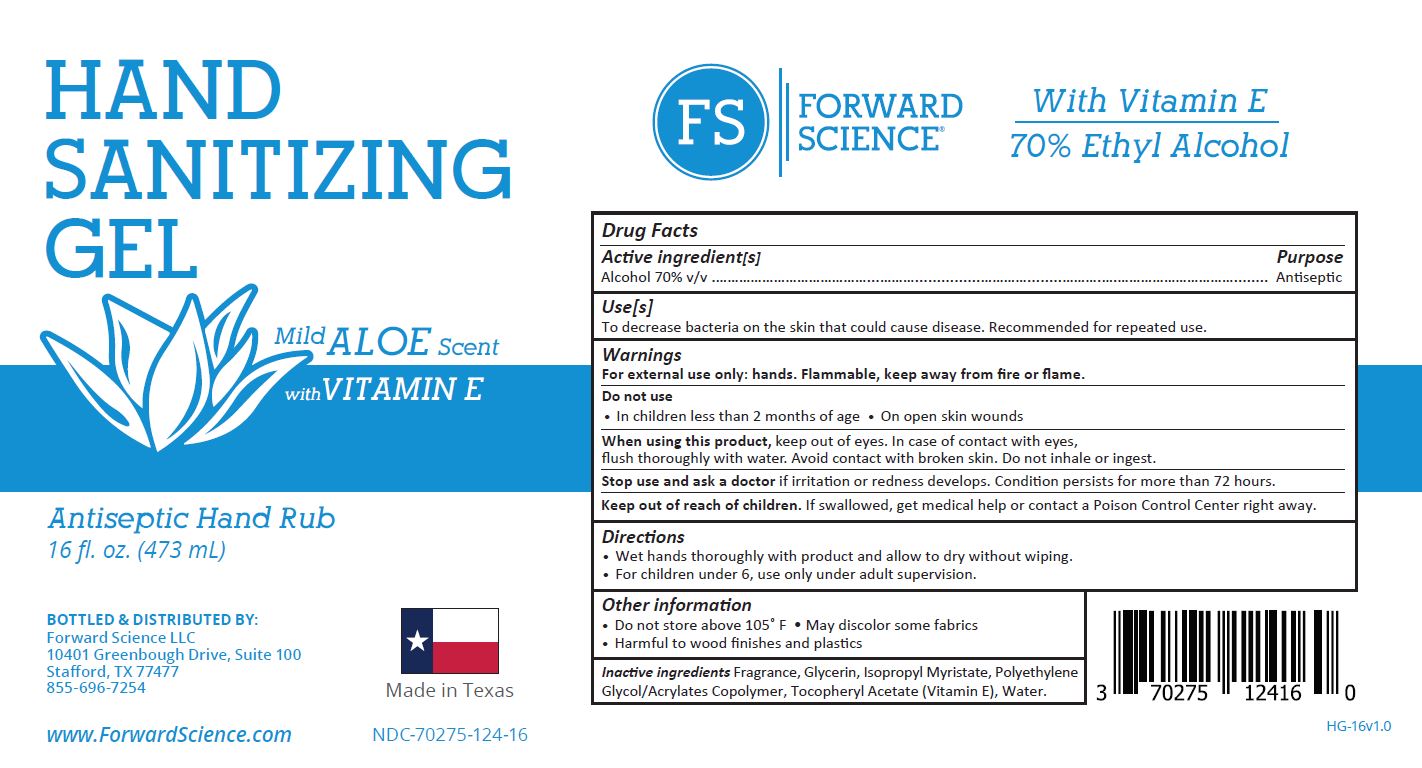 DRUG LABEL: Hand Sanitizing Gel
NDC: 70275-124 | Form: GEL
Manufacturer: Forward Science Technologies LLC
Category: otc | Type: HUMAN OTC DRUG LABEL
Date: 20201006

ACTIVE INGREDIENTS: ALCOHOL 70 mL/100 mL
INACTIVE INGREDIENTS: RAPIDGEL EZ1; ISOPROPYL MYRISTATE; .ALPHA.-TOCOPHEROL ACETATE, DL-; GLYCERIN; WATER

Hand Sanitizer

Active Ingredient(s)

Alcohol 70% v/v

Do Not Use

- In children less than 2 months of age
- On open skin wounds

Keep out of reach of children

If swallowed, get medical help or contact a Poison Control Center right away.

Purpose

Antiseptic

Stop use and ask a doctor if

- irritation or redness develops
- condition persists for more than 72 hours

When using this product

keep out of eyes. In case of contact with eyes, flush thoroughly with water. Avoid with contact with broken skin. Do not inhale or ingest.

Warnings

For external use only: hands. Flammable, keep away from fire or flame.

Other information

Do not store above 105ºF

May discolor some fabrics

Harmful to wood finishes and plastics

Use(s)

To decrease bacteria on the skin that coould cuase disease. Recommended for repeated use.

Directions

Wet hands thouroughly with product and allow to dry without wiping.

For children under 6, use only under adult supervision.

Inactive Ingredients

Fragrance, Glycerin, Isopropyl Myristate, Polyethylene Glycol/Acrylates Copolymer, Tocopheryl Acetate, Water